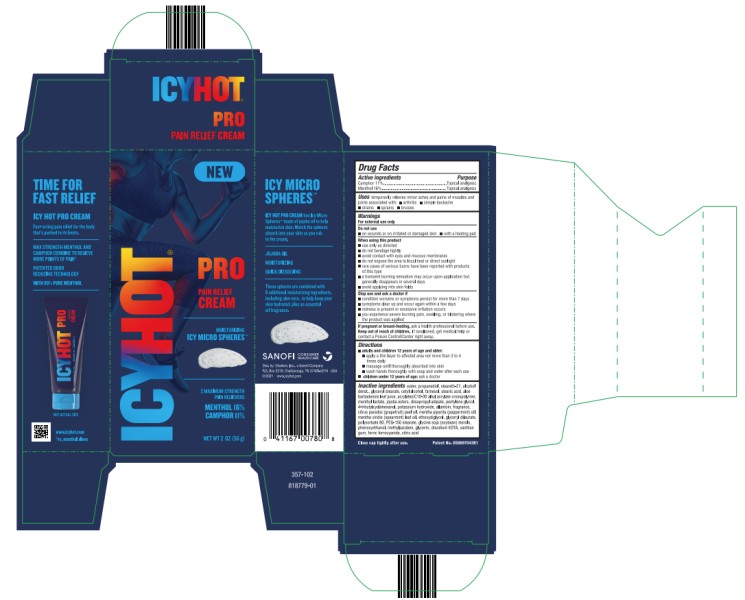 DRUG LABEL: Icy Hot Pro Pain Relief Cream w/ microbeads
NDC: 41167-0078 | Form: CREAM
Manufacturer: Chattem, Inc.
Category: otc | Type: HUMAN OTC DRUG LABEL
Date: 20260114

ACTIVE INGREDIENTS: MENTHOL 0.16 g/1 g; CAMPHOR (SYNTHETIC) 0.11 g/1 g
INACTIVE INGREDIENTS: WATER; PROPANEDIOL; STEARETH-21; ALCOHOL; GLYCERYL MONOSTEARATE; CETOSTEARYL ALCOHOL; FARNESOL; STEARIC ACID; ALOE VERA LEAF; CARBOMER INTERPOLYMER TYPE A (ALLYL SUCROSE CROSSLINKED); PENTYLENE GLYCOL; 4-TERT-BUTYLCYCLOHEXANOL; POTASSIUM HYDROXIDE; ALLANTOIN; GRAPEFRUIT OIL; PEPPERMINT OIL; SPEARMINT OIL; JOJOBA OIL; MENTHYL LACTATE, (-)-; FERRIC FERROCYANIDE; DIISOPROPYL ADIPATE; DIETHYLENE GLYCOL MONOETHYL ETHER; GLYCERYL DILAURATE; POLYSORBATE 80; PEG-150 STEARATE; SOY STEROL; PHENOXYETHANOL; METHYLPARABEN; GLYCERIN; EDETATE DISODIUM ANHYDROUS; XANTHAN GUM; CITRIC ACID MONOHYDRATE

Icy Hot Pro Pain Relief Cream with microbeads

ICY HOT PRO CREAM

Drug Facts

Active ingredients

Camphor 11%, Menthol 16%

Purpose

Topical analgesic

Uses

temporarily relieves minor aches and pains of muscles and joints associated with: ■ arthritis ■ simple backache ■ strains ■ sprains ■ bruises

Warnings

For external use only

Do not use

■ on wounds or on irritated or damaged skin

■ with a heating pad

When using this product

■ use only as directed

■ do not bandage tightly

■ avoid contact with eyes and mucous membranes

■ do not expose the area to local heat or direct sunlight

■ rare cases of serious burns have been reported with products of this type

■ a transient burning sensation may occur upon application but generally disappears in several days

■ avoid applying into skin folds

Stop use and ask a doctor if

■ condition worsens or symptoms persist for more than 7 days

■ symptoms clear up and occur again within a few days

■ redness is present or excessive skin irritation occurs

■ you experience severe burning pain, swelling, or blistering where the product was applied

Keep out of reach of children.

If swallowed, get medical help or contact a Poison Control Center right away.

Directions

- adults and children 12 years of age and older:
  ▪ apply a thin layer to affected area not more than 3 to 4 times daily
  ▪ massage until thoroughly absorbed into skin
  ▪ wash hands thoroughly with soap and water after each use
- children under 12 years of age: ask a doctor

Inactive ingredients

water, propanediol, steareth-21, alcohol denat., glyceryl stearate, cetyl alcohol, farnesol, stearic acid, aloe barbadensis leaf juice, acrylates/C10-30 alkyl acrylate crosspolymer, menthyl lactate, jojoba esters, diisopropyl adipate, pentylene glycol, 4-t-butylcyclohexanol, potassium hydroxide, allantoin, fragrance, citrus paradisi (grapefruit) peel oil, mentha piperita (peppermint) oil, mentha viridis (spearmint) leaf oil, ethoxydiglycol, glyceryl dilaurate, polysorbate 80, PEG-150 stearate, glycine soja (soybean) sterols, phenoxyethanol, methylparaben, glycerin, disodium EDTA, xanthan gum, ferric ferrocyanide, citric acid

357-102

Close cap tightly after use.

Keep carton as it contains important information.

PRINCIPAL DISPLAY PANEL

IcyHot
Pro Pain Relief Cream
Net Wt 2 OZ (56 g)